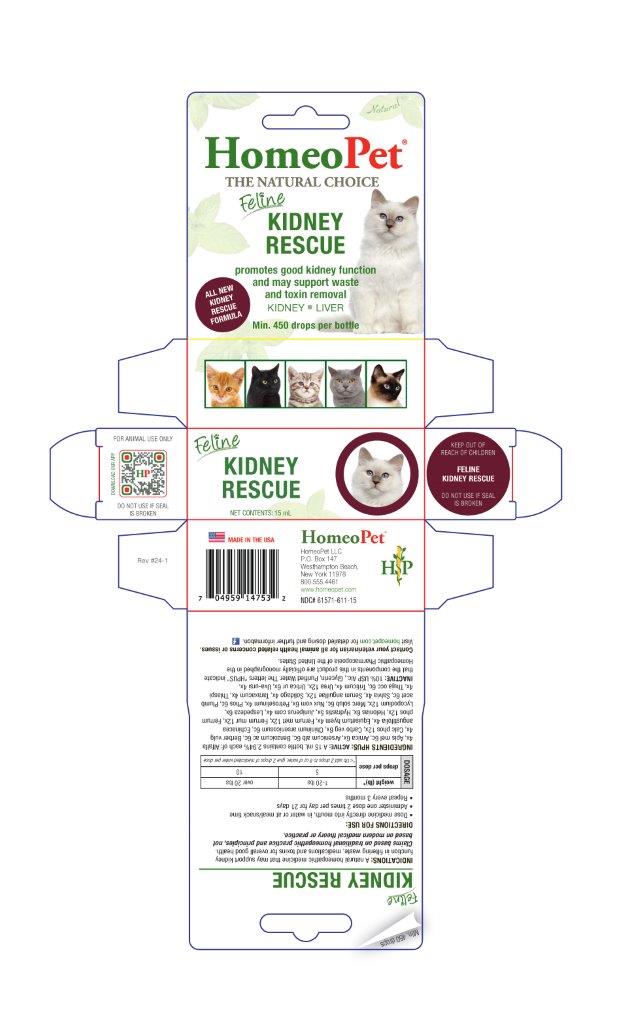 DRUG LABEL: Kidney Rescue
NDC: 61571-611 | Form: LIQUID
Manufacturer: HomeoPet, LLC
Category: homeopathic | Type: OTC ANIMAL DRUG LABEL
Date: 20241121

ACTIVE INGREDIENTS: MEDICAGO SATIVA WHOLE 4 [hp_X]/15 mL; APIS MELLIFERA 6 [hp_C]/15 mL; ARNICA MONTANA WHOLE 6 [hp_X]/15 mL; ARSENIC TRIOXIDE 6 [hp_C]/15 mL; BENZOIC ACID 6 [hp_C]/15 mL; BERBERIS VULGARIS ROOT BARK 4 [hp_X]/15 mL; TRIBASIC CALCIUM PHOSPHATE 12 [hp_X]/15 mL; ACTIVATED CHARCOAL 6 [hp_X]/15 mL; QUININE ARSENITE 6 [hp_C]/15 mL; ECHINACEA ANGUSTIFOLIA WHOLE 4 [hp_X]/15 mL; EQUISETUM HYEMALE WHOLE 4 [hp_X]/15 mL; IRON 12 [hp_X]/15 mL; FERROSOFERRIC PHOSPHATE 12 [hp_X]/15 mL; CHAMAELIRIUM LUTEUM ROOT 6 [hp_X]/15 mL; GOLDENSEAL 5 [hp_X]/15 mL; JUNIPER BERRY 4 [hp_X]/15 mL; LESPEDEZA CAPITATA FLOWERING TOP 6 [hp_X]/15 mL; LYCOPODIUM CLAVATUM SPORE 12 [hp_X]/15 mL; MERCURIUS SOLUBILIS 6 [hp_C]/15 mL; STRYCHNOS NUX-VOMICA SEED 6 [hp_X]/15 mL; PETROSELINUM CRISPUM WHOLE 4 [hp_X]/15 mL; PHOSPHORUS 6 [hp_C]/15 mL; LEAD ACETATE ANHYDROUS 6 [hp_C]/15 mL; SAGE 4 [hp_X]/15 mL; ANGUILLA ROSTRATA BLOOD SERUM 12 [hp_X]/15 mL; SOLIDAGO VIRGAUREA FLOWERING TOP 4 [hp_X]/15 mL; TARAXACUM OFFICINALE 4 [hp_X]/15 mL; CAPSELLA BURSA-PASTORIS WHOLE 4 [hp_X]/15 mL; THUJA OCCIDENTALIS LEAFY TWIG 6 [hp_C]/15 mL; ELYMUS REPENS ROOT 4 [hp_X]/15 mL; UREA 12 [hp_X]/15 mL; URTICA URENS WHOLE 6 [hp_X]/15 mL; ARCTOSTAPHYLOS UVA-URSI LEAF 4 [hp_X]/15 mL
INACTIVE INGREDIENTS: ALCOHOL; GLYCERIN; WATER

Kidney Rescue

PURPOSE

promotes good kidney function and may support waste and toxin removal

Direction for Use and Dosing:

- Dose medicine directly into mouth, in water or at meal/snack time
- Administer one dose 2 times per day for 21 days
- Repeat every 3 months

Dosage:

Dosage | weight (lb)* | 1-20 lbs | over 20 lbs
Dosage | drops per dose | 5 | 10
Dosage | drops per dose | *<1 lb add 2 drops to 8 oz of water, give 2 drops of medicated water per dose

ASK DOCTOR

Contact your veterinarian for all animal health related concerns or issues.

Visit homeopet.com for detailed dosing and further information.

Ingredients HPUS: Active

Alfalfa 4x, Apis mel 6c, Arnica 6x, Arsenicum alb 6c, Benzoicum ac 6c, Berber vulg 4x, Calc phos 12x, Carbo veg 6x, Chininum arsenicosum 6c, Echinacea angustifolia 4x, Equisetum hyem 4x, Ferrum met 12x, Ferrum mur 12x, Ferrum phos 12x, Helonias 6x, Hydrastis 5x, Juniperus com 4x, Lespedeza 6x, Lycopodium 12x, Merc solub 6c, Nux vom 6x, Petroselinum 4x, Phos 6c, Plumb acet 6c, Salvia 4x, Serum anguillae 12x, Solidago 4x, Taraxacum 4x, Thlaspi 4x, Thuja occ 6c, Triticum 4x, Urea 12x, Urtica ur 6x, Uva-ursi 4x.

Inactive Ingredients

USP Alcohol, Glycerin, Purified Water

INDICATIONS:

A natural homeopathic medicine that may support kidney function in filtering waste, medications and toxins for overall good health. Claims based on traditional homeopathic practice and principles, not based on modern medical theory or practice.

PACKAGE LABEL

Add image transcription here...